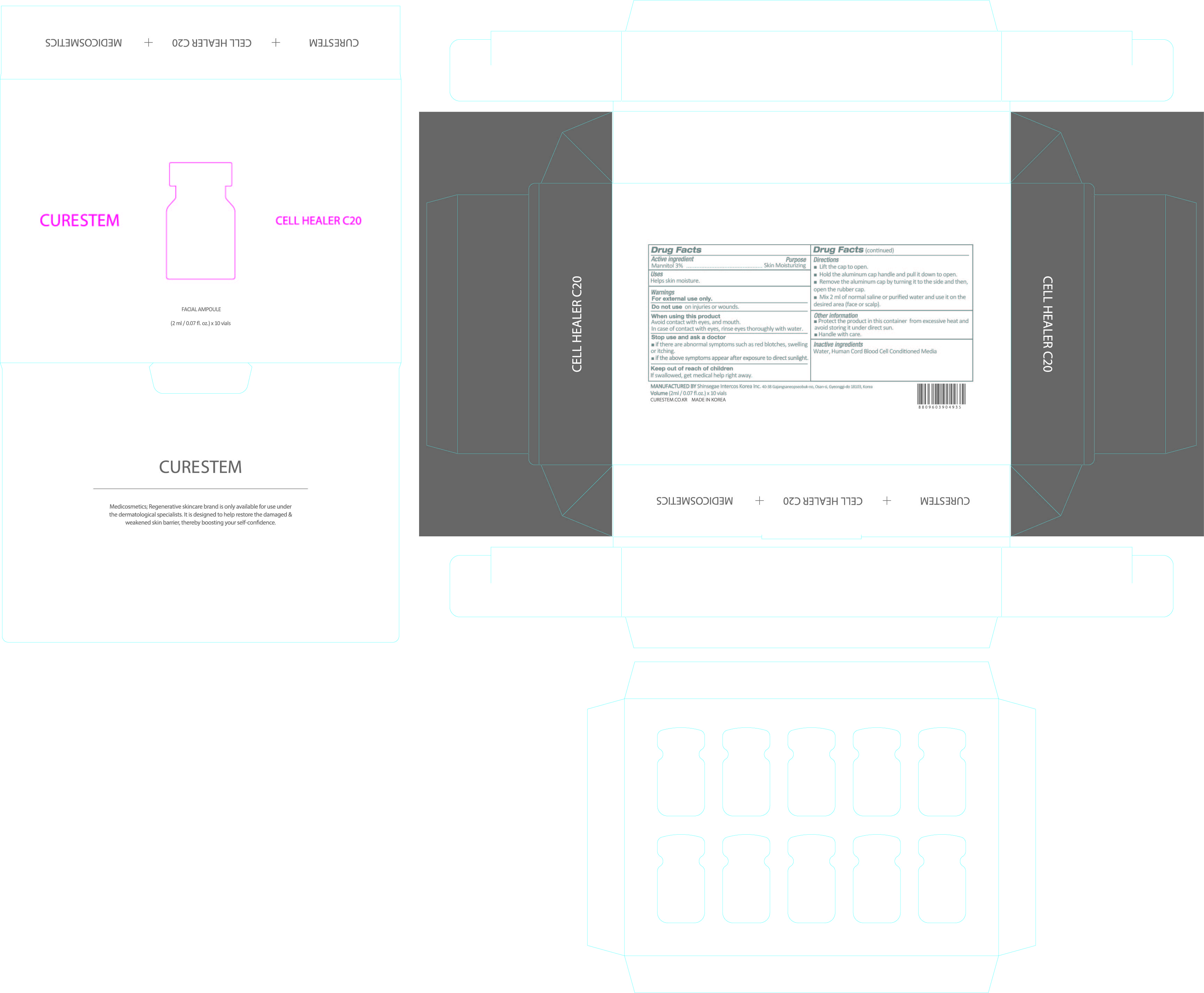 DRUG LABEL: CURESTEM CELL HEALER C20
NDC: 78521-020 | Form: POWDER
Manufacturer: DNK CORPORATION LTD.
Category: otc | Type: HUMAN OTC DRUG LABEL
Date: 20200605

ACTIVE INGREDIENTS: MANNITOL 0.06 g/2 mL
INACTIVE INGREDIENTS: CORD BLOOD; WATER

CURESTEM CELL HEALER C20 : 78521-020-10

Active ingredient

Mannitol 3%

Purpose

Skin Moisturizing

Uses

Helps skin moisture.

Warnings

For external use only.

Do not use

on injuries or wounds.

When using this product

Avoid contact with eyes, and mouth.

In case of contact with eyes, rinse eyes thoroughly with water.

Stop use and ask a doctor

■ if there are abnormal symptoms such as red blotches, swelling or itching.

■ if the above symptoms appear after exposure to direct sunlight.

Keep out of reach of children

If swallowed, get medical help or contact a Poison Control Center right away.

Directions

■ Lift the cap to open.
■ Hold the aluminum cap handle and pull it down to open.
■ Remove the aluminum cap by turning it to the side and then,
open the rubber cap.
■ Mix 2 ml of normal saline or purified water and use it on the
desired area (face or scalp).

Other information

■ Protect the product in this container from excessive heat and avoid storing it under direct sun.

■ Handle with care.

Inactive ingredients

Water, Human Cord Blood Cell Conditioned Media